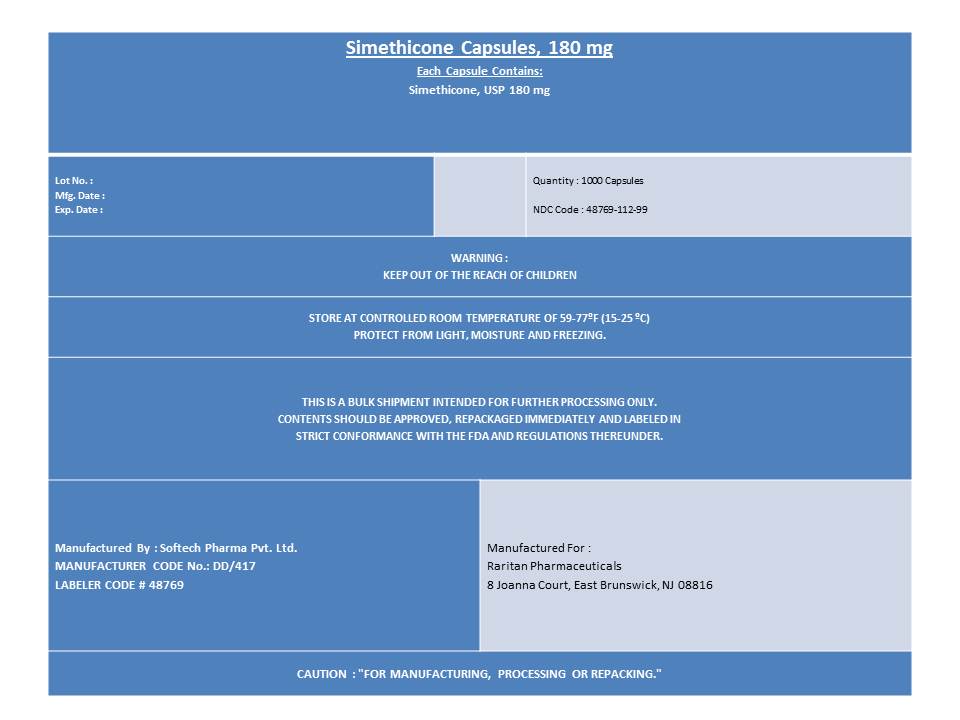 DRUG LABEL: SIMETHICONE
NDC: 48769-112 | Form: CAPSULE, LIQUID FILLED
Manufacturer: Softech Pharma Pvt. Ltd.
Category: otc | Type: HUMAN OTC DRUG LABEL
Date: 20120629

ACTIVE INGREDIENTS: DIMETHICONE 180 mg/1 1
INACTIVE INGREDIENTS: FD&C RED NO. 40; FD&C YELLOW NO. 6; GELATIN; GLYCERIN

SIMETHICONE Capsules 180 mg

Active ingredient (in each softgel)

Simethicone 180 mg

Purpose

Antigas

Uses

Relieves bloating, pressure or fullness commonly referred to as gas

Warnings

Stop use and ask doctor if condition persists

Keep out of Reach of Children

Directions

- Swallow one or two softgels as needed after a meal
- Do not exceed two softgels per day except under the advise and supervision of a physician

Other Information

- Each softgel contains: potassium 5 mg
- Store at 20^0 - 25^0C

Inactive ingredients:

FD and C Red No. 40, FD and C yellow No. 6, Gelatin, Glycerol